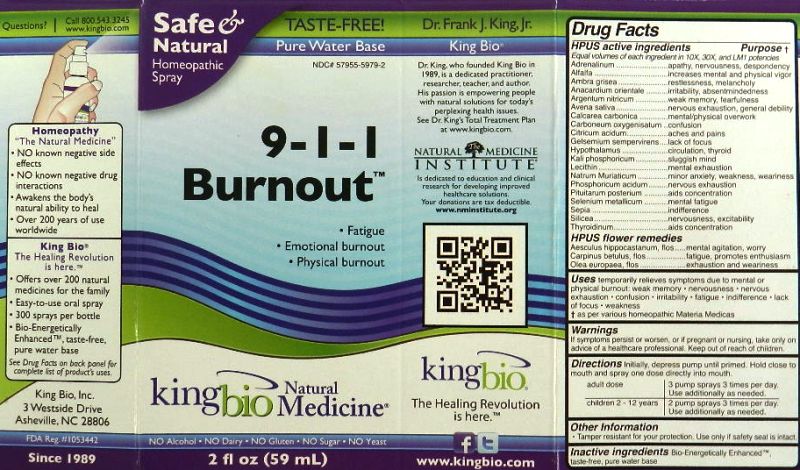 DRUG LABEL: 9-1-1 Burnout
NDC: 57955-5979 | Form: LIQUID
Manufacturer: King Bio Inc.
Category: homeopathic | Type: HUMAN OTC DRUG LABEL
Date: 20111114

ACTIVE INGREDIENTS: EPINEPHRINE 10 [hp_X]/59 mL; ALFALFA 10 [hp_X]/59 mL; AMBERGRIS 10 [hp_X]/59 mL; SEMECARPUS ANACARDIUM JUICE 10 [hp_X]/59 mL; SILVER NITRATE 10 [hp_X]/59 mL; AVENA SATIVA FLOWERING TOP 10 [hp_X]/59 mL; OYSTER SHELL CALCIUM CARBONATE, CRUDE 10 [hp_X]/59 mL; ANHYDROUS CITRIC ACID 10 [hp_X]/59 mL; CARBON MONOXIDE 10 [hp_X]/59 mL; GELSEMIUM SEMPERVIRENS ROOT 10 [hp_X]/59 mL; BOS TAURUS HYPOTHALAMUS 10 [hp_X]/59 mL; POTASSIUM PHOSPHATE, DIBASIC 10 [hp_X]/59 mL; EGG PHOSPHOLIPIDS 10 [hp_X]/59 mL; SODIUM CHLORIDE 10 [hp_X]/59 mL; PHOSPHORIC ACID 10 [hp_X]/59 mL; SUS SCROFA PITUITARY GLAND 10 [hp_X]/59 mL; SELENIUM 10 [hp_X]/59 mL; SEPIA OFFICINALIS JUICE 10 [hp_X]/59 mL; SILICON DIOXIDE 10 [hp_X]/59 mL; THYROID, UNSPECIFIED 10 [hp_X]/59 mL; AESCULUS HIPPOCASTANUM FLOWER 10 [hp_X]/59 mL; CARPINUS BETULUS FLOWERING TOP 10 [hp_X]/59 mL; OLEA EUROPAEA FLOWER 10 [hp_X]/59 mL
INACTIVE INGREDIENTS: WATER

9-1-1 Burnout

Active Ingredients

HPUS active ingredients

Adrenalinum

Alfalfa

Ambra grisea

Anacardium orientale

Argentum nitricum

Avena sativa

Calcarea carbonica

Carboneum oxygenisatum

Citricum acidum

Gelsemium sempervirens

Hypothalamus

Kali phosphoricum

Lecithin

Natrum Muriaticum

Phosphoricum acidum

Pituitarum posterium

Selenium metallicum

Sepia

Silicea

Thyroidinum

HPUS flower remedies

Aesculus hippocastanum, flos

Carpinus betulus, flos

Olea europaea, flos

Reference image burnout.jpg

Inactive Ingredient

Bio-Energetically Enhanced taste-free, pure water base.

Reference image burnout.jpg

Purpose section

HPUS active ingredients

Adrenalinum.............................apathy, nervousness, despondency

Alfalfa......................................increases mental and physical vigor

Ambra grisea...........................restlessness, melancholy

Anacardium orientale................irritability, absentmindedness

Argentum nitricum....................weak memory, fearfulness

Avena sativa............................nervous exhaustion, general debility

Calcarea carbonica...................mental / physical overwork

Carboneum oxygenisatum........confusion

Citricum acidum......................aches and pains

Gelsemium sempervirens.........lack of focus

Hypothalamus.........................circulation, thyroid

Kali phosphoricum...................sluggish mind

Lecithin...................................mental exhaustion

Natrum muriaticum...................minor anxiety, weakness, weariness

Phosphoricum acidum..............nervous exhaustion

Pituitarum posterium.................aids concentration

Selenium metallicum.................mental fatigue

Sepia......................................indifference

Silicea....................................nervousness, excitability

Thyroidinum............................aids concentration

HPUS flower remedies

Aesculus hippocastanum, flos.....mental agitation, worry

Carpinus betulus, flos.................fatigue, promotes enthusiasm

Olea europaea, flos....................exhaustion and weariness

Reference image burnout.jpg

Indications and usage

Uses temporarily relieves symptoms due to mental or physical burnout:

- weak memory
- nervousness
- nervous exhaustion
- confusion
- irritability
- fatigue
- indifference
- lack of focus
- weakness

as per various homeopathic Materia Medicas
Reference image burnout.jpg

Dosage and Administration

Directions: Initially, depress pump until primed. Hold close to mouth and spray one dose directly into mouth.

Adult Dose 3 pump sprays 3 times per day. Use additionally as needed.

Children 2-12 years 2 pump sprays 3 times per day. Use additionally as needed.

Reference image burnout.jpg

Warnings

If symptoms persist or worsen, or if pregnant or nursing, take only on advice of a healthcare professional. Keep out of reach of children.

Reference image burnout.jpg

Keep Out Of Reach Of Children

Reference image burnout.jpg

PACKAGE LABEL

King Bio Inc.
3 Westside Drive
Asheville, NC 28806

www.kingbio.com

Reference image burnout.jpg